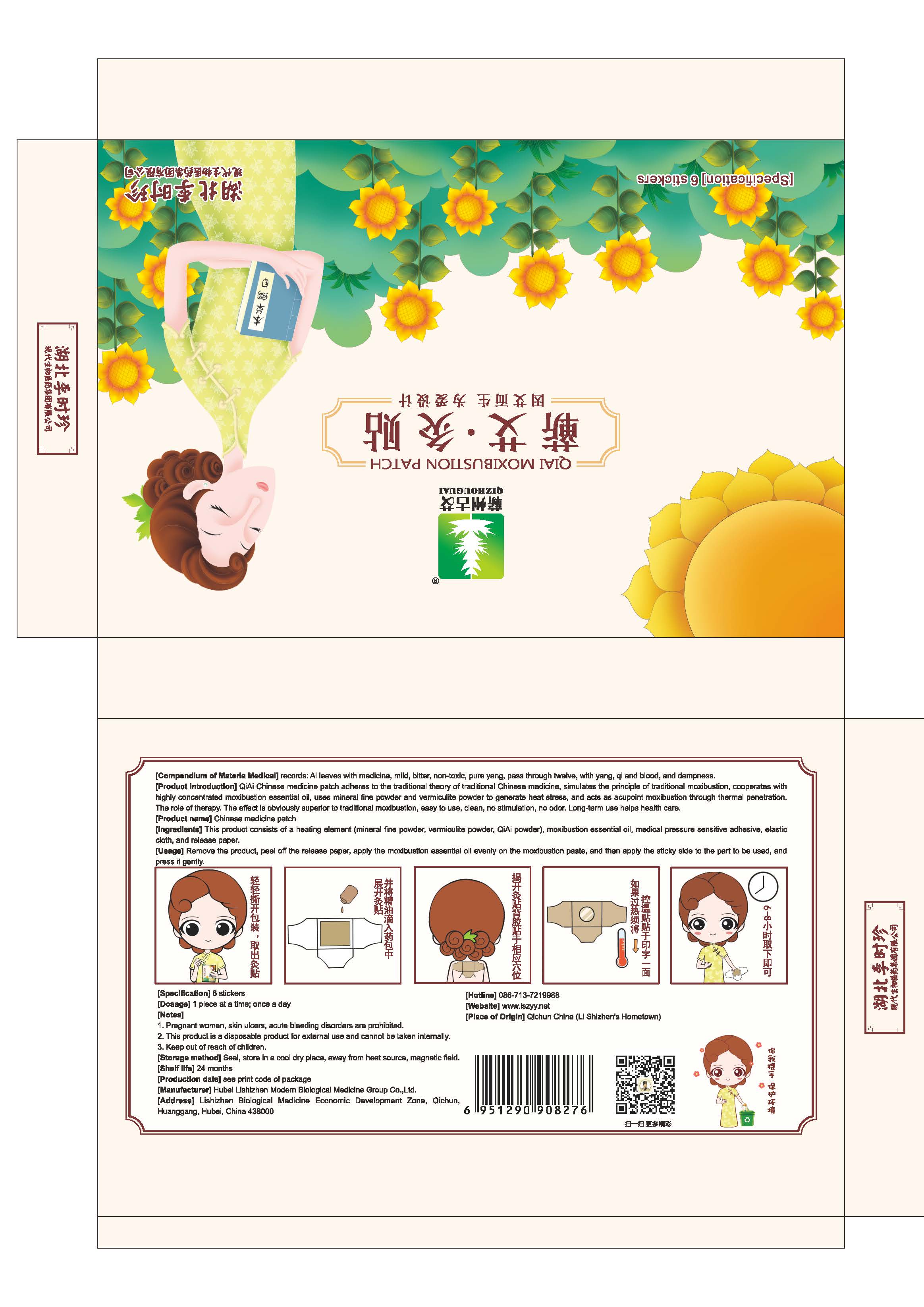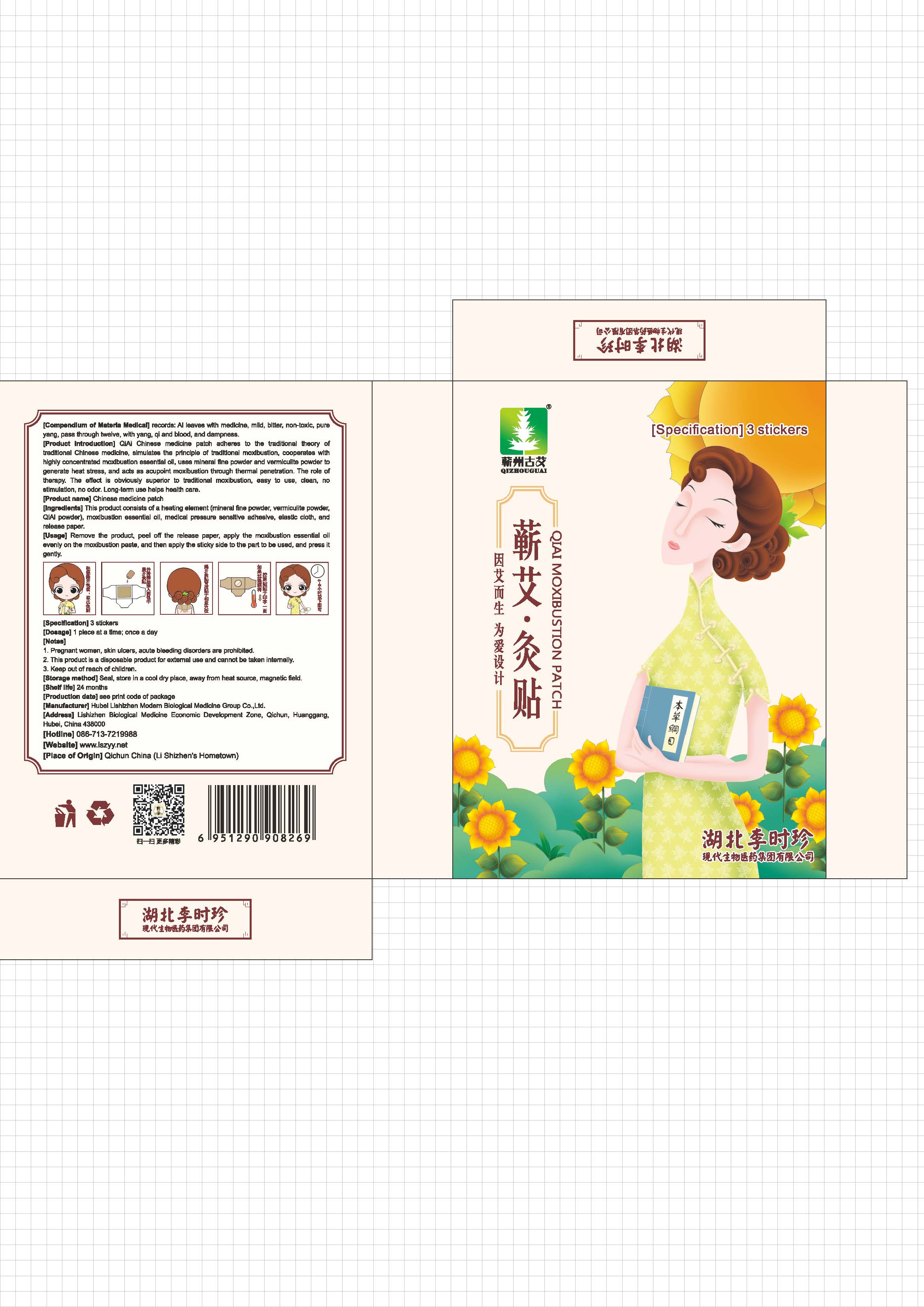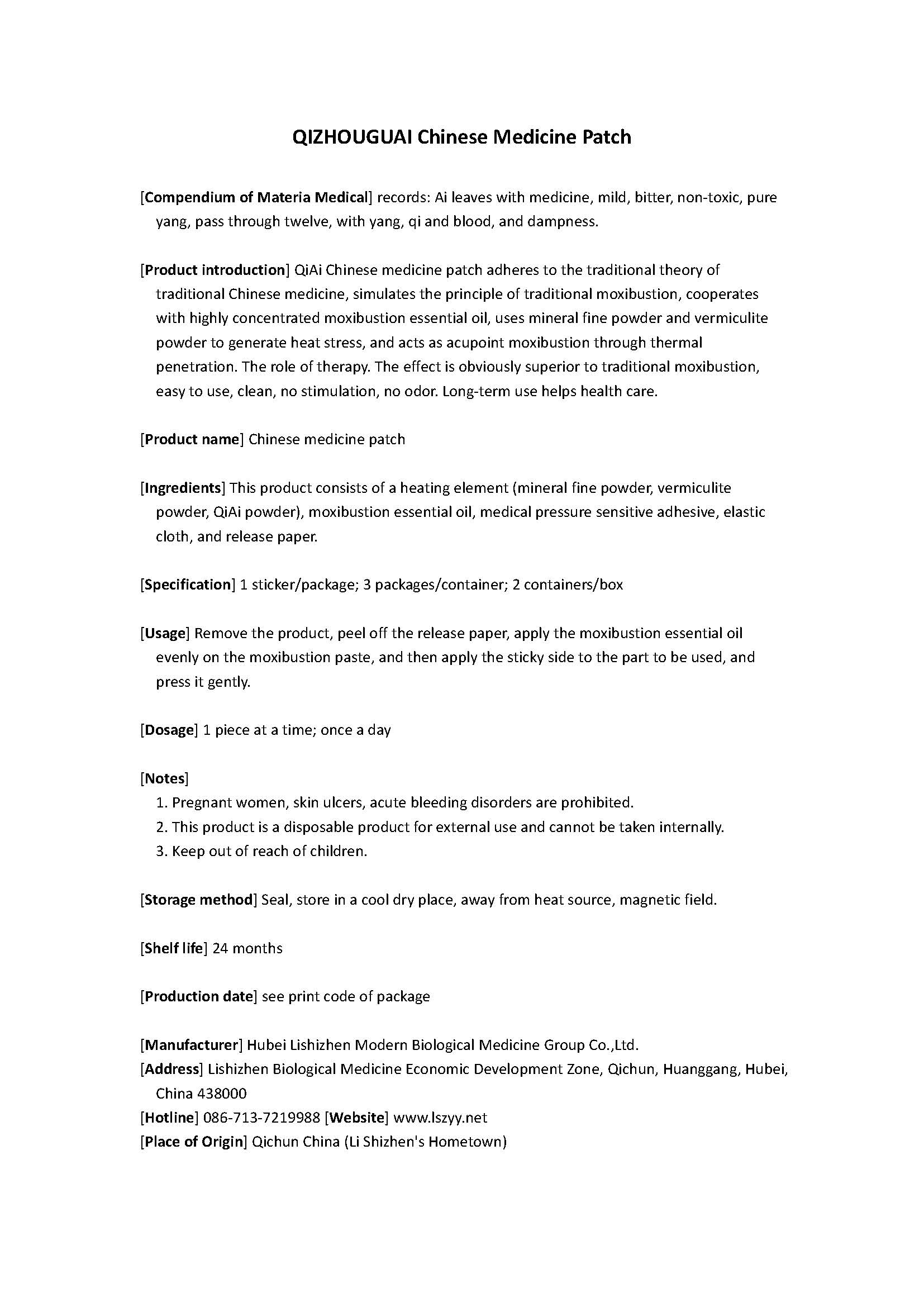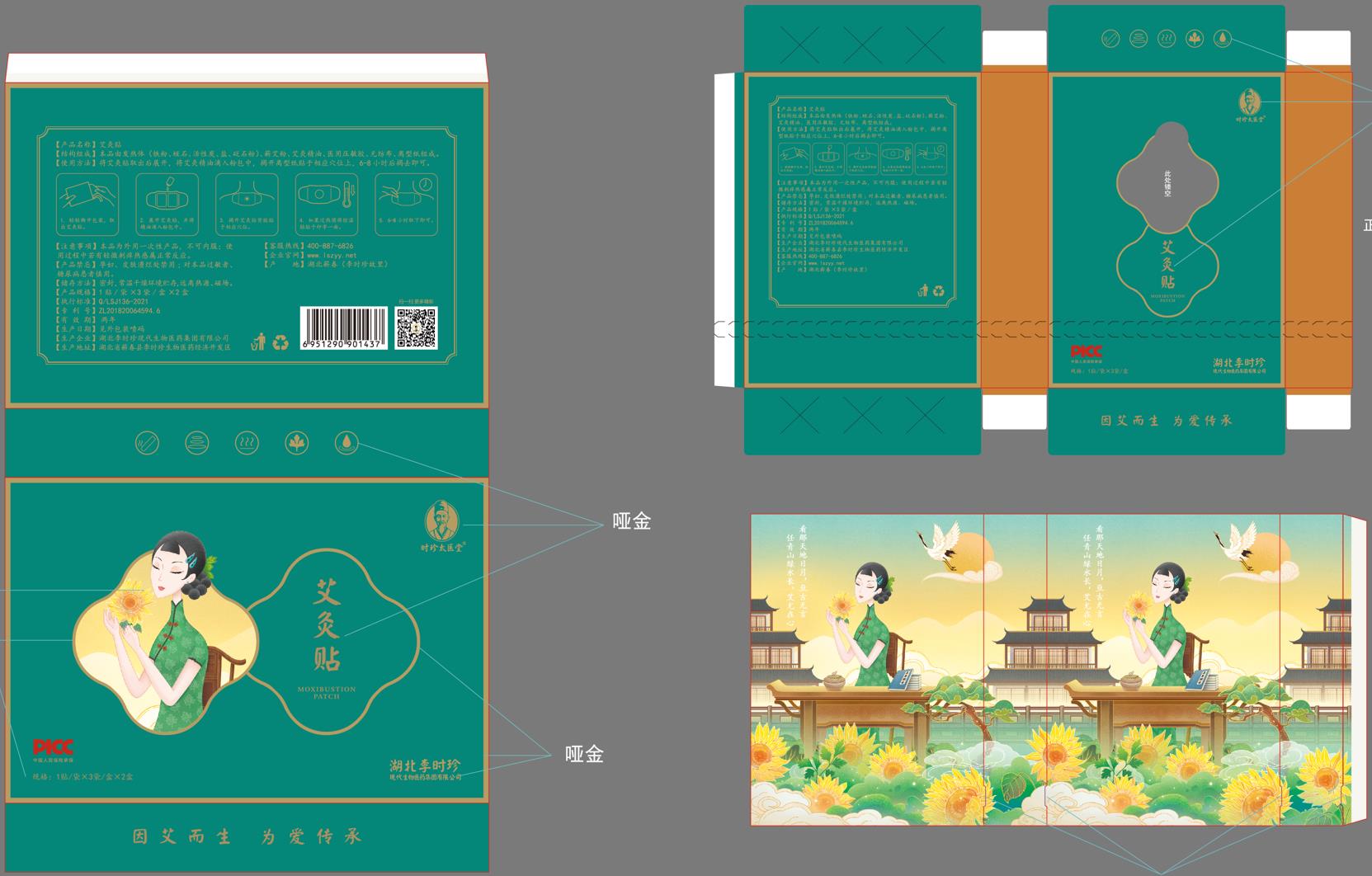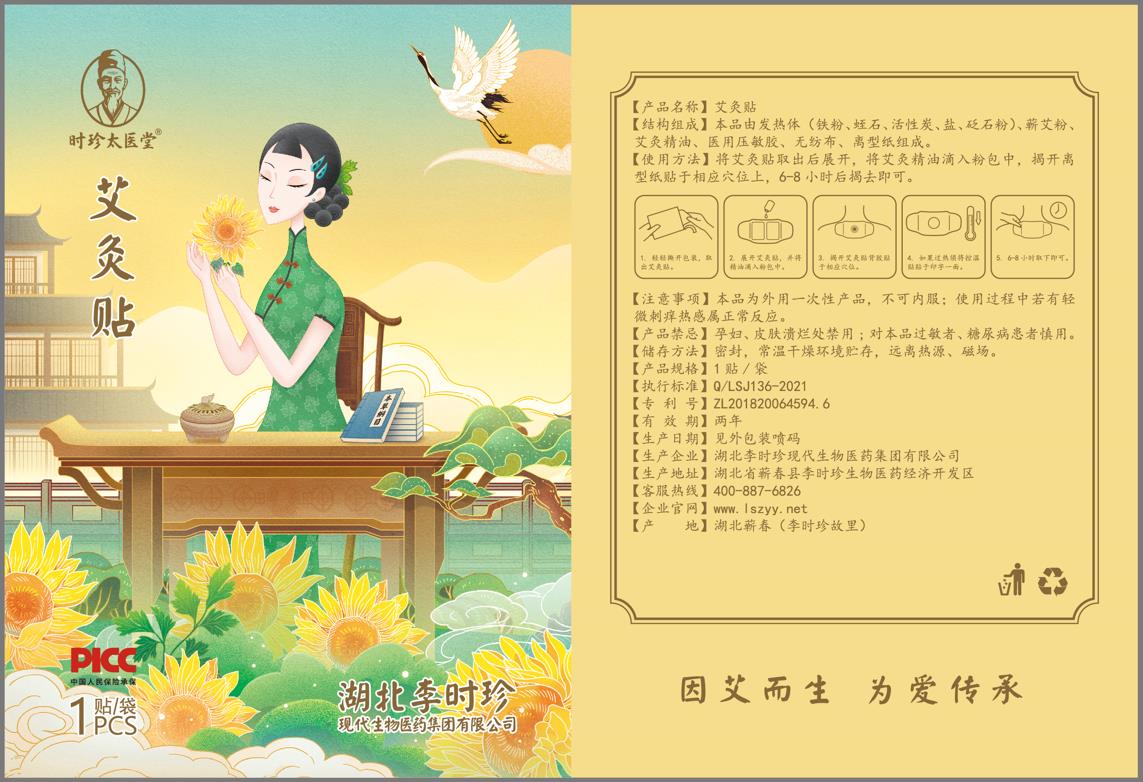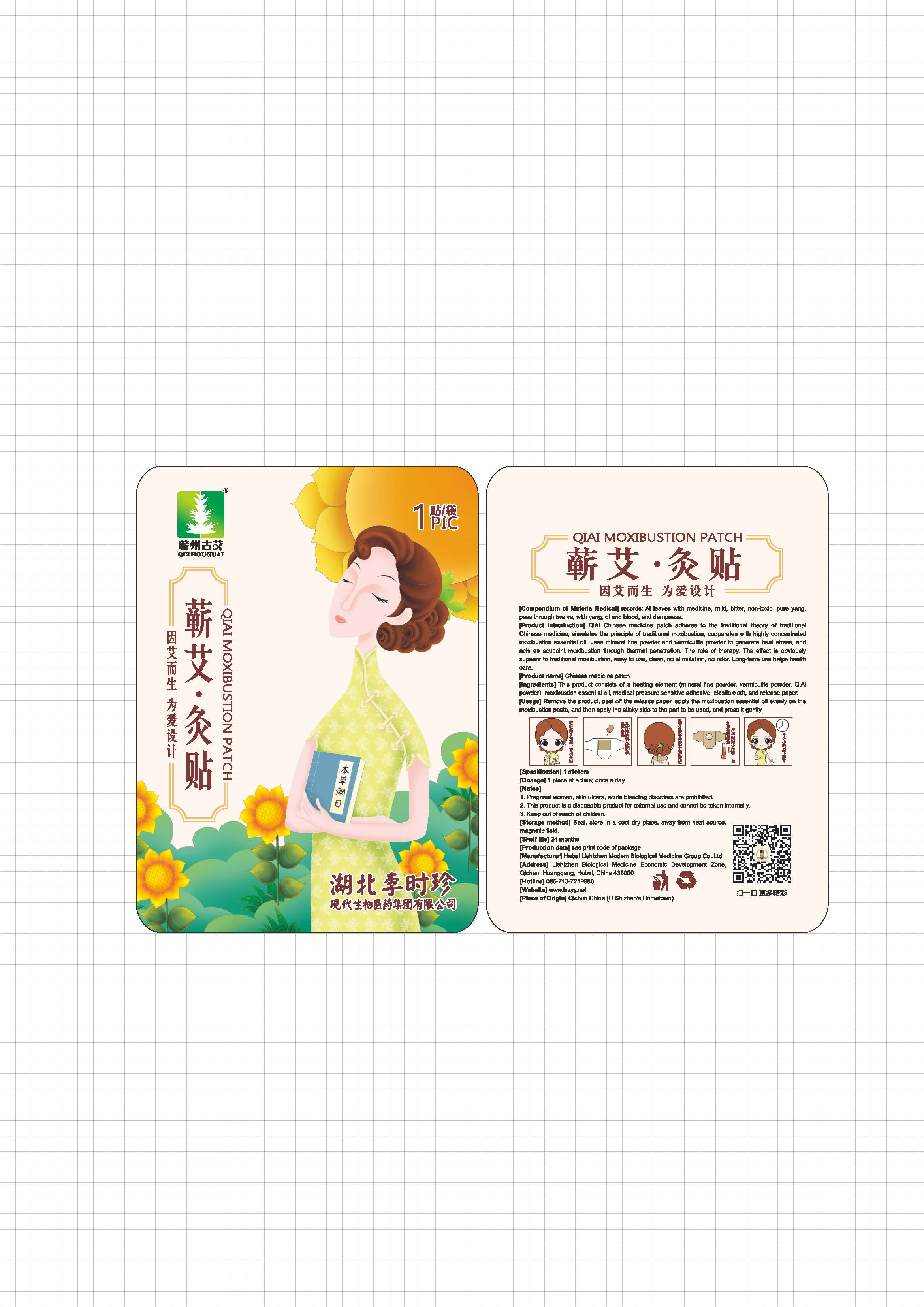 DRUG LABEL: ShiZhenTaiYiTang Moxibustion Patch
NDC: 72624-526 | Form: TAPE
Manufacturer: Hubei Lishizhen Modern Biological Medicine Group Co.,Ltd.
Category: otc | Type: HUMAN OTC DRUG LABEL
Date: 20221013

ACTIVE INGREDIENTS: BUTYLENE GLYCOL 0.2 g/1 g
INACTIVE INGREDIENTS: HYDROXYETHYL CELLULOSE (280 MPA.S AT 2%); WATER; PHENOXYETHANOL; POLYETHYLENE GLYCOL 300000; CHLORPHENESIN

ShiZhenTaiYiTang Moxibustion Patch

Active ingredient

butylene glycol 20%) w/w (0.2g/package)

Inactive ingredient

water

hydroxyethylcellulose

polyethylene glycol 300000

phenoxyethanol

chlorphenesin

Purpose

It is a heat disposable paster incorporating chemicals that provides heat therapy for body.

When using

Conditioning neck, back, hands and feet and other rheumatism pain and spleen and stomach caused by cold injury, deficiency diarrhea and other conditions.

Do not use

If irritation or discomfort occurs, discontinue the use and consult a physician.

Stop use

If irritation or discomfort occurs, discontinue the use and consult a physician.

Ask doctor

If irritation or discomfort occurs, discontinue the use and consult a physician.

Ask doctor/pharmacist when you current use other drugs.

Keep out of reach of children and away from eyes and ears.

Questions

Please contact us when you have any questions.

Pregnancy or breast feeding

Pregnant or breast feeding women shall follow doctor advice.

Indications & usage

Pain relief, hot release, warming uterus, hemostatic, can be used to improve the conditioning neck, back, hands and feet and other rheumatism pain and spleen and stomach caused by cold injury, deficiency diarrhea and other conditions.

Apply one paster on stomach venter.

Dosage & administration

One time one patch.

Dosage forms & strengths

Its dosage form is patch.

A patch one time, or reapply as needed.

One gram in one patch.

The active ingredient strength is 20% w/w.

Warnings

If irritation or discomfort occurs, discontinue the use and consult a physician.

Very slippery on surfaces, clean spills immediately.

Keep out of reach of children and pets.